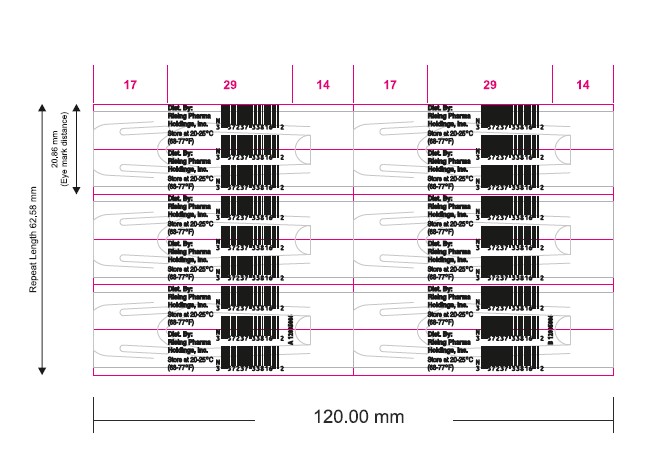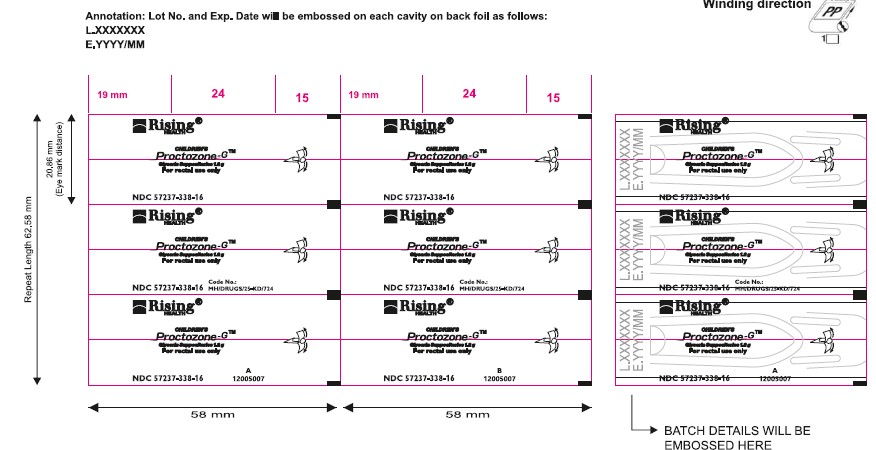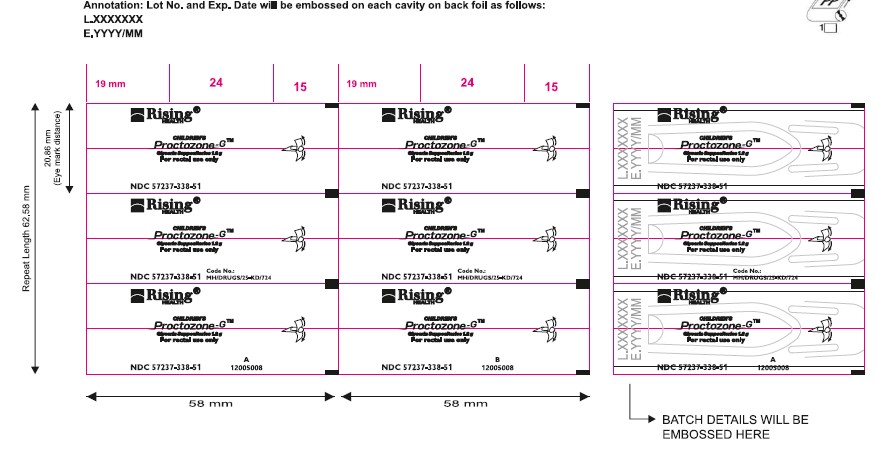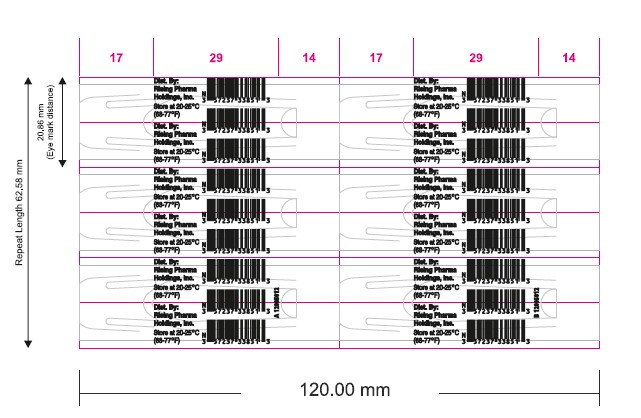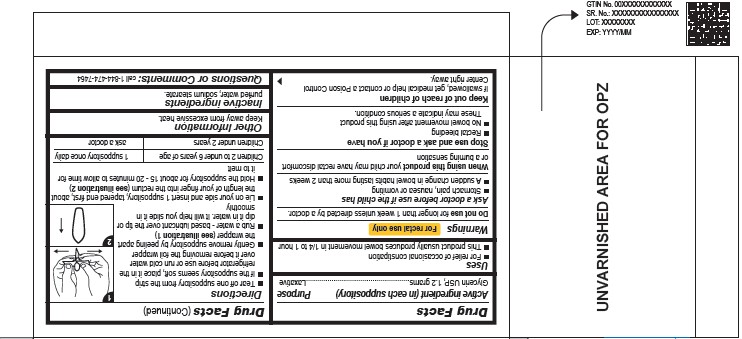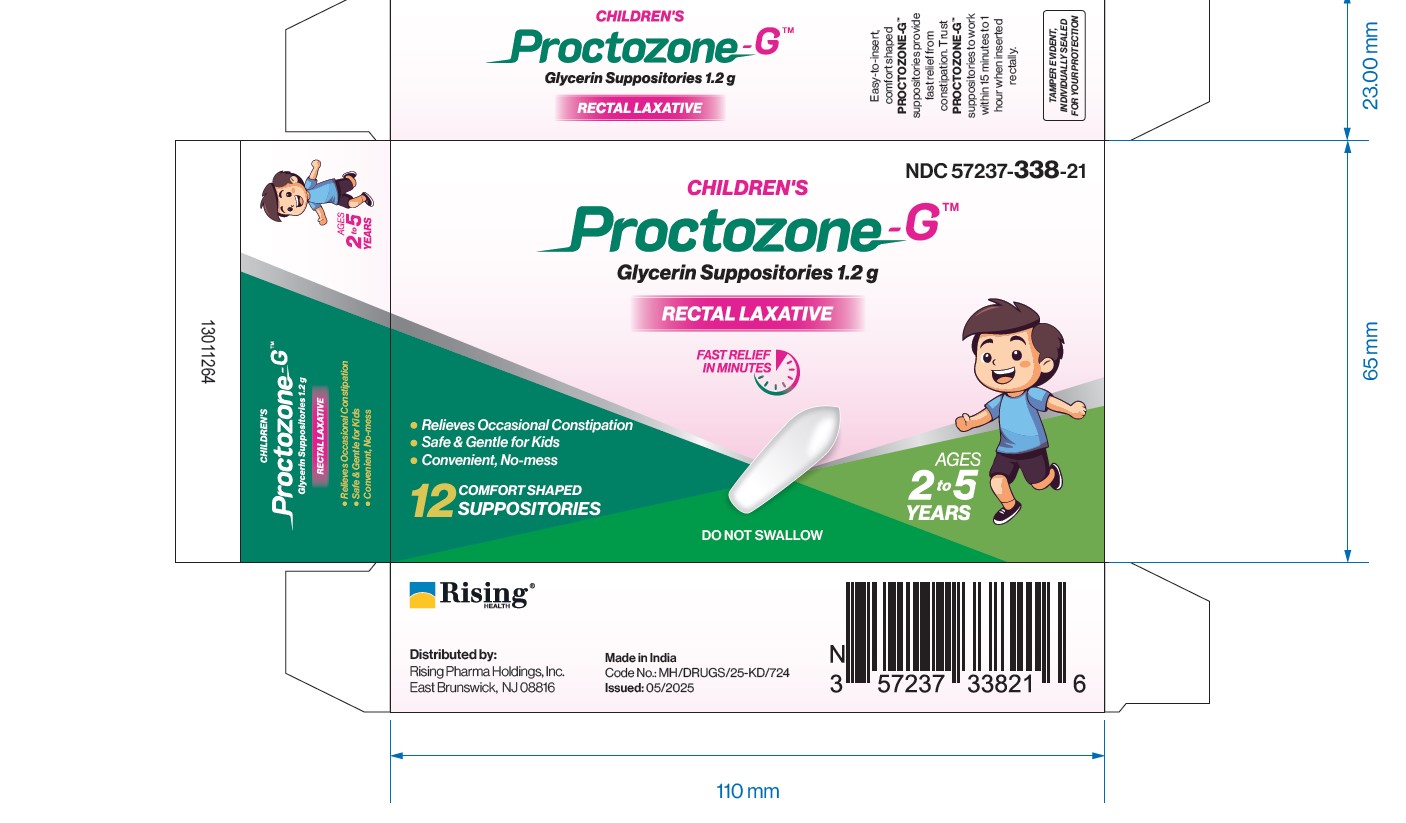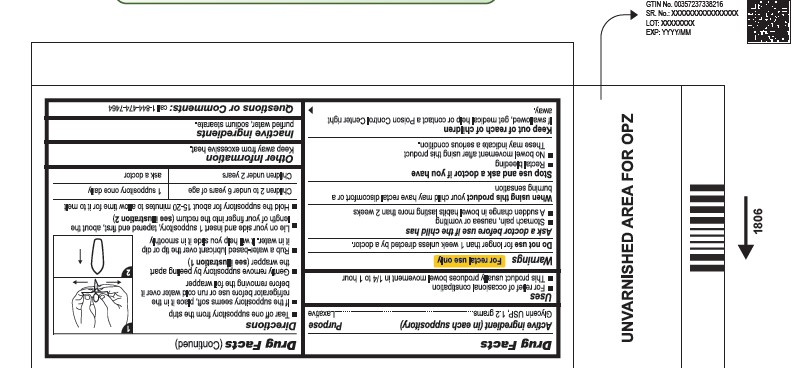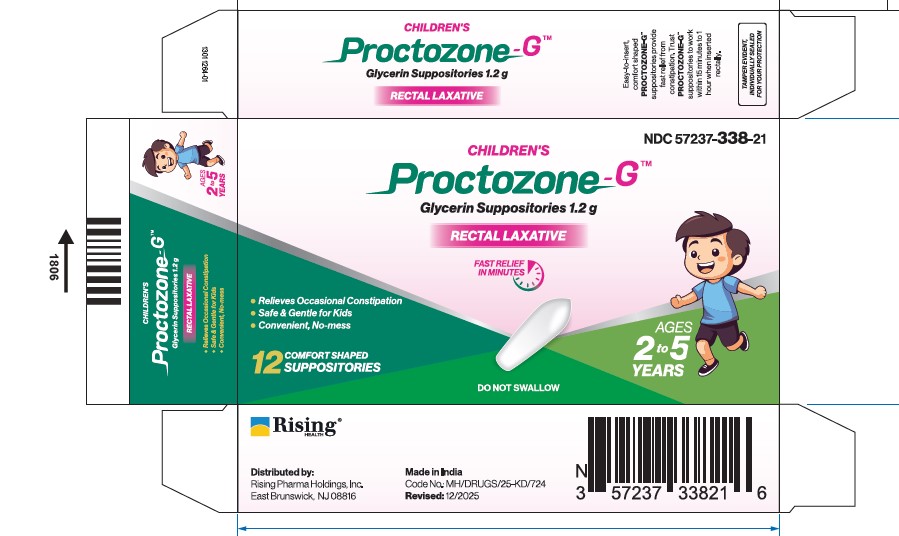 DRUG LABEL: Proctozone-G
NDC: 57237-338 | Form: SUPPOSITORY
Manufacturer: Rising Pharma Holdings, Inc.
Category: otc | Type: HUMAN OTC DRUG LABEL
Date: 20260106

ACTIVE INGREDIENTS: GLYCERIN 1.2 g/1 1
INACTIVE INGREDIENTS: WATER; SODIUM STEARATE

Proctozone-GTM Glycerin Suppositories 1.2 g

Drug Facts

Active ingredient (in each suppository)

Glycerin USP, 1.2 grams

Purpose

Laxative

Uses

- For relief of occasional constipation
- This product usually produces bowel movement in 1/4 to 1 hour

Warnings

For rectal use only

Do not use for longer than 1 week unless directed by a doctor.

Ask a doctor before use if the child has

- Stomach pain, nausea or vomiting
- A sudden change in bowel habits lasting more than 2 weeks

When using this product your child may have rectal discomfort or a burning sensation

Stop use and ask a doctor if you have

- Rectal bleeding
- No bowel movement after using this product
  These may indicate a serious condition.

Keep out of reach of children

If swallowed, get medical help or contact a Poison Control Center right away.

Directions

- Tear off one suppository from the strip
- If the suppository seems soft, place it in the refrigerator before use or run cold water over it before removing the foil wrapper
- Gently remove suppository by peeling apart the wrapper (see illustration 1)
- Rub a water-based lubricant over the tip or dip it in water. It will help you slide it in smoothly
- Lie on your side and insert 1 suppository, tapered end first, about the length of your finger into the rectum (see illustration 2)
- Hold the suppository for about 15-20 minutes to allow time for it to melt
- Children 2 to under 6 years of age ...................... 1 suppository once daily
- Children under 2 years ............................................ ask a doctor

Other Information

Keep away from excessive heat.

Inactive ingredients

purified water, sodium stearate.

Questions or Comments:

call 1-844-474-7464

TAMPER EVIDENT, INDIVIDUALLY SEALED FOR YOUR PROTECTION

Distributed by:
Rising Pharma Holdings, Inc.
East Brunswick, NJ 08816

Made in India

Code No.: MH/DRUGS/25-KD/724

Issued: 05/2025

PACKAGE LABEL

NDC 57237-338-21 (2 blisters of 6 suppositories)

Proctozone-GTM

GLYCERIN SUPPOSITORIES 1.2 g

RECTAL LAXATIVE

Front Foil (57237-338-16)

Back Foil (57237-338-16)

NDC 57237-338-52 (5 blisters of 5 suppositories)

Front Foli (57237-338-51)

Back Foil (57237-338-51)